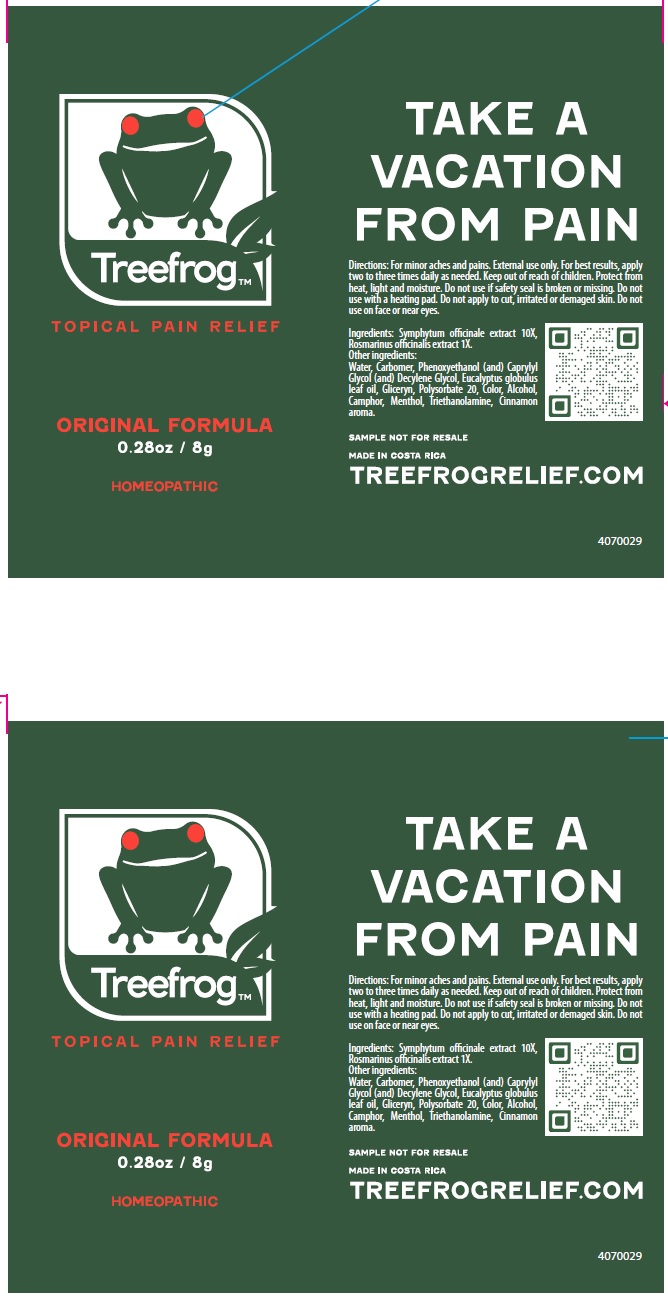 DRUG LABEL: Tree frog
NDC: 55715-006 | Form: GEL
Manufacturer: Laboratorios Zepol S.A.
Category: homeopathic | Type: HUMAN OTC DRUG LABEL
Date: 20231201

ACTIVE INGREDIENTS: COMFREY ROOT 10 [hp_X]/1 g; ROSEMARY 1 [hp_X]/1 g
INACTIVE INGREDIENTS: WATER; CARBOMER HOMOPOLYMER, UNSPECIFIED TYPE; PHENOXYETHANOL; CAPRYLYL GLYCOL; EUCALYPTUS GLOBULUS LEAF; ALCOHOL; MENTHOL, UNSPECIFIED FORM; TROLAMINE; POLYSORBATE 20; CAMPHOR (NATURAL); CINNAMON; DECYLENE GLYCOL

Tree frog

Directions:

PURPOSE

For minor aches and pains

DOSAGE AND ADMINISTRATION

External use only. For best results, apply two to three times daily as needed.

WARNINGS SECTION

Keep out of reach of children.

Protect from heat, light and moisture. Do not use if safety seal is broken or missing. Do not use with a heating pad. Do not apply to cut, irritated or demaged skin. Do not use on face or near eyes.

Ingredients:

Symphytum officinale extract 10X,

Rosmarinus officinale extract 1X.

Other ingredients:

Water, Carbomer, Phenoxyethanol (and) Caprylyl Glycol (and) Decylene Glycol, Eucalyptus globulus leaf oil, Gliceryn, Polysorbate 20, Color, Alcohol, Camphor, Menthol, Triethanolamine, Cinnamon aroma.